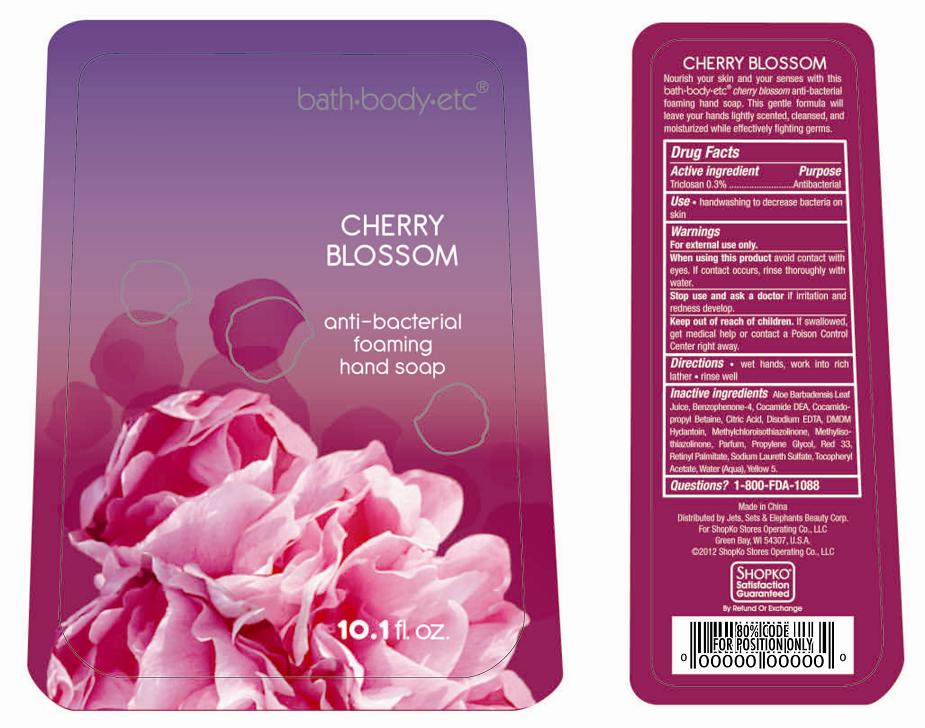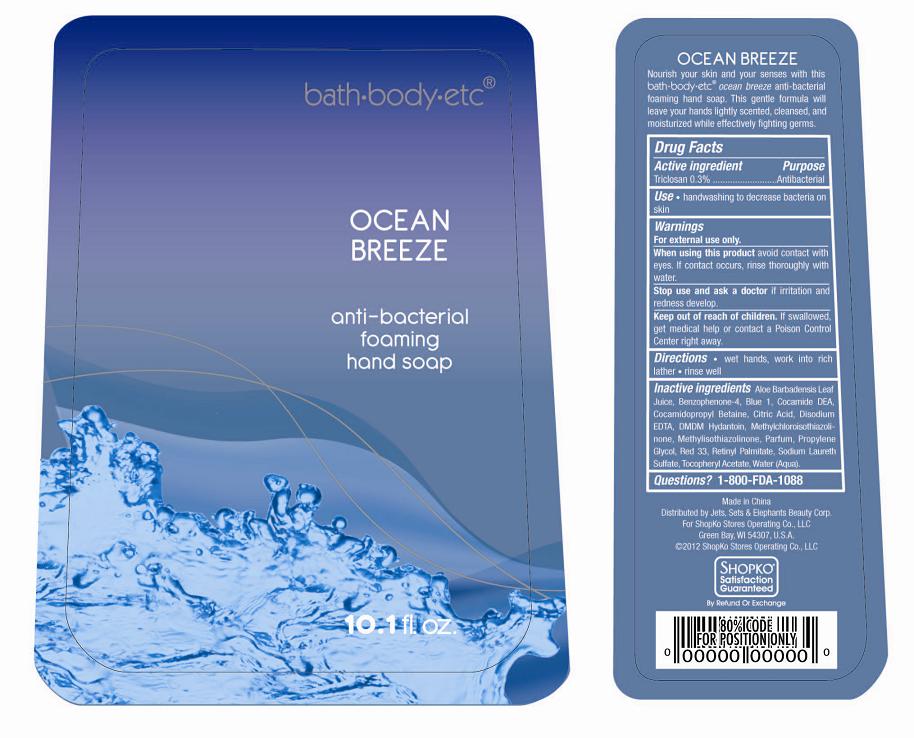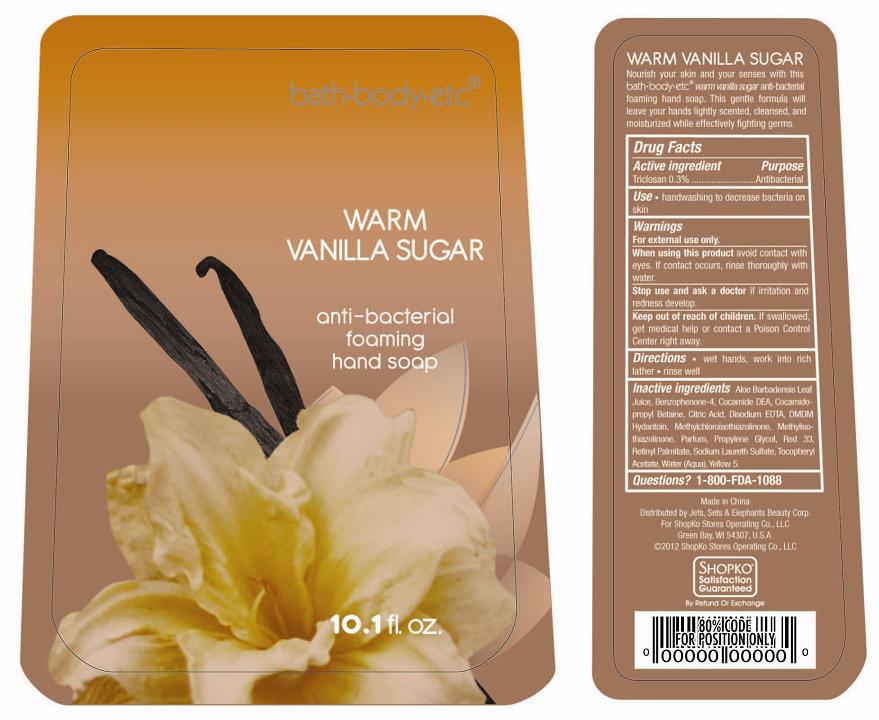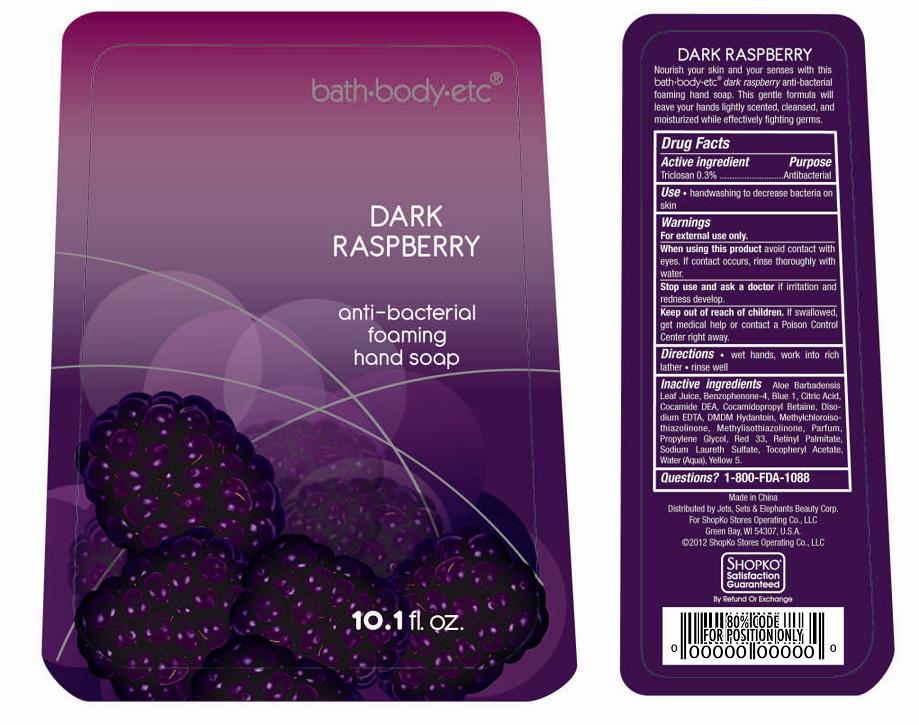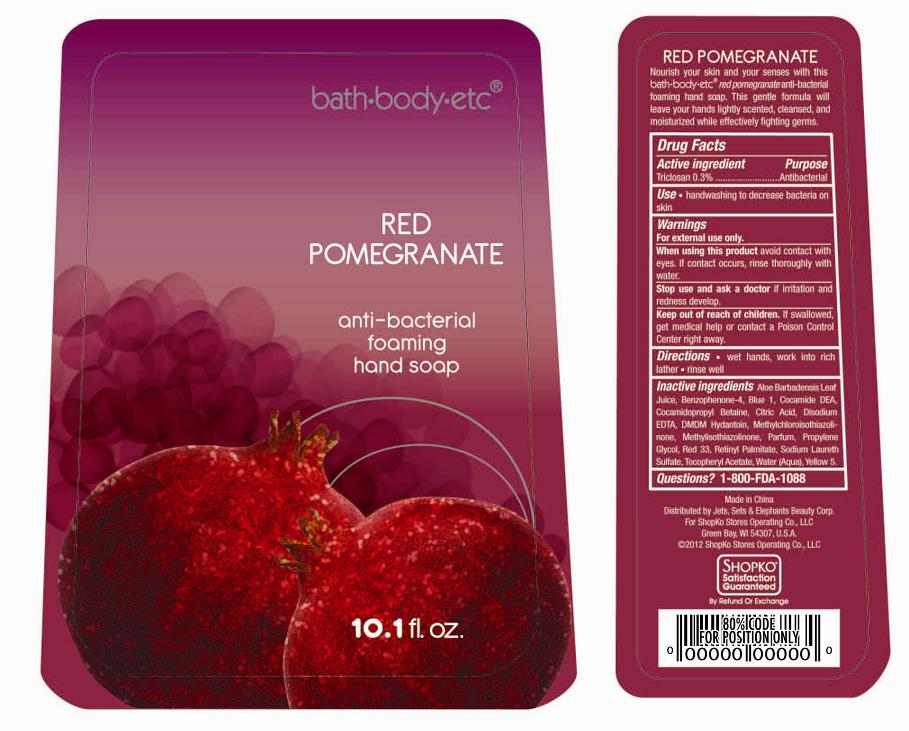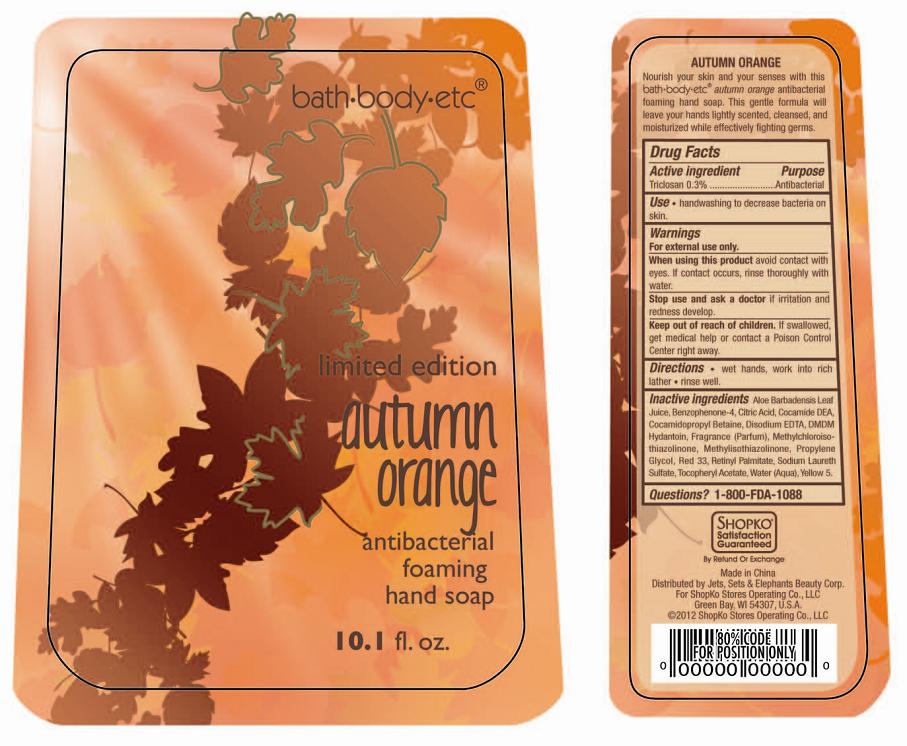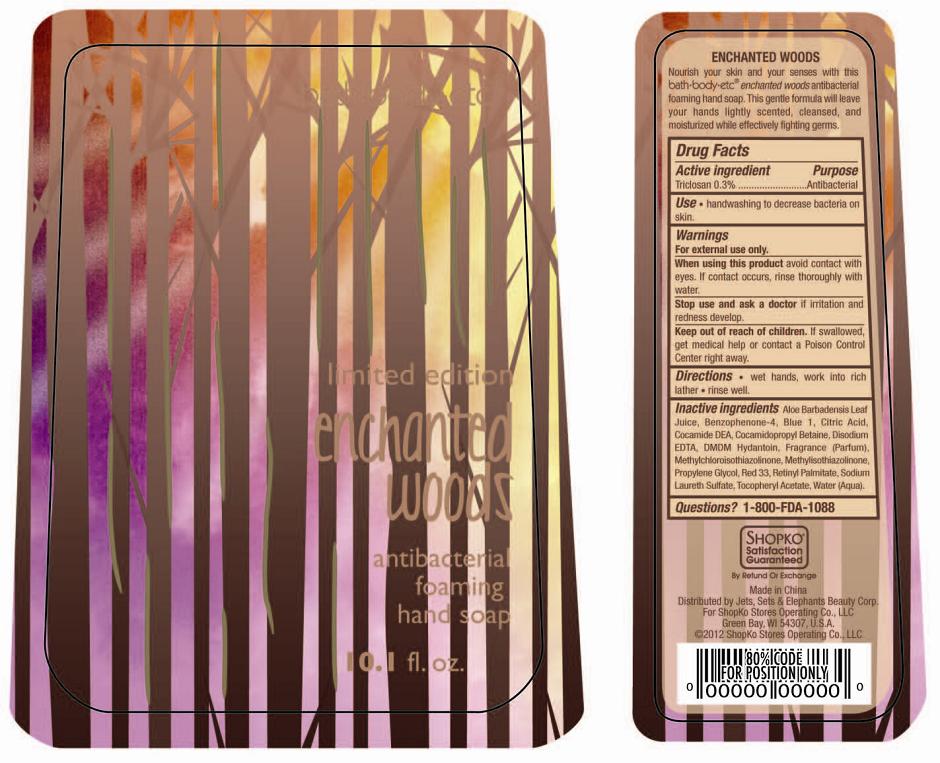 DRUG LABEL: Shopko Antibacterial Foaming Hand Sanitizer
NDC: 50988-296 | Form: GEL
Manufacturer: Jets, Sets, & Elephants Beauty Corp.
Category: otc | Type: HUMAN OTC DRUG LABEL
Date: 20120807

ACTIVE INGREDIENTS: TRICLOSAN 3 mg/1 mL
INACTIVE INGREDIENTS: WATER; SODIUM LAURETH SULFATE; COCAMIDOPROPYL BETAINE; COCO DIETHANOLAMIDE; PROPYLENE GLYCOL; DMDM HYDANTOIN; ALOE VERA LEAF; METHYLISOTHIAZOLINONE; METHYLCHLOROISOTHIAZOLINONE; ACETYL TRIETHYLHEXYL CITRATE; EDETATE DISODIUM; SULISOBENZONE; .ALPHA.-TOCOPHEROL ACETATE; VITAMIN A PALMITATE; D&C RED NO. 33; FD&C YELLOW NO. 5

SHOPKO® Anti-Bacterial Foaming Hand Soap - Cherry Blossom, Ocean Breeze, Warm Vanilla Sugar, Dark Raspberry, Red Pomegranate, Autumn Orange, Enchanted Woods

Active ingredient

Triclosan 0.3%

Purpose

Antibacterial

Use

- handwashing to decrease bacteria on skin

Warnings

For external use only.

When using this product

avoid contact with eyes. If contact occurs, rinse thoroughly with water.

Stop use and ask a doctor

if irritation and redness develop.

Keep out of reach of children.

If swallowed, get medical help or contact a Poison Control Center right away.

Directions

- wet hands, work into rich lather
- rinse well

Inactive ingredients (Cherry Blossom)

Aloe Barbadensis Leaf Juice, Benzophenone-4, Cocamide DEA, Cocamidopropyl Betaine, Citric Acid, Disodium EDTA, DMDM Hydantoin, Methylchloroisothiazolinone, Methylisothiazolinone, Fragrance (Parfum), Propylene Glycol, Red 33, Retinyl Palmitate, Sodium Laureth Sulfate, Tocopheryl Acetate, Water (Aqua), Yellow 5.

Inactive ingredients (Ocean Breeze)

Aloe Barbadensis Leaf Juice, Benzophenone-4, Blue 1, Cocamide DEA, Cocamidopropyl Betaine, Citric Acid, Disodium EDTA, DMDM Hydantoin, Methylchloroisothiazolinone, Methylisothiazolinone, Fragrance (Parfum), Propylene Glycol, Red 33, Retinyl Palmitate, Sodium Laureth Sulfate, Tocopheryl Acetate, Water (Aqua).

Inactive ingredients (Warm Vanilla Sugar)

Aloe Barbadensis Leaf Juice, Benzophenone-4, Cocamide DEA, Cocamidopropyl Betaine, Citric Acid, Disodium EDTA, DMDM Hydantoin, Methylchloroisothiazolinone, Methylisothiazolinone, Fragrance (Parfum), Propylene Glycol, Red 33, Retinyl Palmitate, Sodium Laureth Sulfate, Tocopheryl Acetate, Water (Aqua), Yellow 5.

Inactive ingredients (Dark Raspberry)

Aloe Barbadensis Leaf Juice, Benzophenone-4, Blue 1, Citric Acid, Cocamide DEA, Cocamidopropyl Betaine, Disodium EDTA, DMDM Hydantoin, Methylchloroisothiazolinone, Methylisothiazolinone, Fragrance (Parfum), Propylene Glycol, Red 33, Retinyl Palmitate, Sodium Laureth Sulfate, Tocopheryl Acetate, Water (Aqua), Yellow 5.

Inactive ingredients (Red Pomegranate)

Aloe Barbadensis Leaf Juice, Benzophenone-4, Blue 1,Cocamide DEA, Cocamidopropyl Betaine, Citric Acid, Disodium EDTA, DMDM Hydantoin, Methylchloroisothiazolinone, Methylisothiazolinone, Parfum, Propylene Glycol, Red 33, Retinyl Palmitate, Sodium Laureth Sulfate, Tocopheryl Acetate, Water (Aqua), Yellow 5.

Inactive ingredients (Autumn Orange)

Aloe Barbadensis Leaf Juice, Benzophenone-4, Citric Acid, Cocamide DEA, Cocamidopropyl Betaine, Disodium EDTA, DMDM Hydantoin, Fragrance (Parfum), Methylchloroisothiazolinone, Methylisothiazolinone, Propylene Glycol, Red 33, Retinyl Palmitate, Sodium Laureth Sulfate, Tocopheryl Acetate, Water (Aqua), Yellow 5.

Inactive ingredients (Enchanted Woods)

Aloe Barbadensis Leaf Juice, Benzophenone-4, Blue 1, Citric Acid, Cocamide DEA, Cocamidopropyl Betaine, Disodium EDTA, DMDM Hydantoin, Fragrance (Parfum), Methylchloroisothiazolinone, Methylisothiazolinone, Propylene Glycol, Red 33, Retinyl Palmitate, Sodium Laureth Sulfate, Tocopheryl Acetate, Water (Aqua).

QUESTIONS?

1-800-FDA-1088

PACKAGE/LABEL PRINCIPAL DISPLAY PANEL

bath·body·etc®

CHERRY BLOSSOM

anti-bacterial foaming hand soap

10.1 fl.oz

Made in China

Distributed by Jets, Sets & Elephants Beauty Corp.

For ShopKo Stores Operating Co., LLC

Green Bay, WI 54307, U.S.A

©2012 ShopKo Stores Operating Co., LLC

SATISFACTION GUARANTEED BY REFUND OR EXCHANGE

Bottle Label

PACKAGE/LABEL PRINCIPAL DISPLAY PANEL

bath·body·etc®

OCEAN BREEZE

anti-bacterial foaming hand soap

10.1 fl.oz

Made in China

Distributed by Jets, Sets & Elephants Beauty Corp.

For ShopKo Stores Operating Co., LLC

Green Bay, WI 54307, U.S.A

©2012 ShopKo Stores Operating Co., LLC

SATISFACTION GUARANTEED BY REFUND OR EXCHANGE

Bottle Label

PACKAGE/LABEL PRINCIPAL DISPLAY PANEL

bath·body·etc®

WARM VANILLA SUGAR

anti-bacterial foaming hand soap

10.1 fl.oz

Made in China

Distributed by Jets, Sets & Elephants Beauty Corp.

For ShopKo Stores Operating Co., LLC

Green Bay, WI 54307, U.S.A

©2012 ShopKo Stores Operating Co., LLC

SATISFACTION GUARANTEED BY REFUND OR EXCHANGE

Bottle Label

PACKAGE/LABEL PRINCIPAL DISPLAY PANEL

bath·body·etc®

DARK RASPBERRY

anti-bacterial foaming hand soap

10.1 fl.oz

Made in China

Distributed by Jets, Sets & Elephants Beauty Corp.

For ShopKo Stores Operating Co., LLC

Green Bay, WI 54307, U.S.A

©2012 ShopKo Stores Operating Co., LLC

SATISFACTION GUARANTEED BY REFUND OR EXCHANGE

Bottle Label

PACKAGE/LABEL PRINCIPAL DISPLAY PANEL

bath·body·etc®

RED POMEGRANATE

anti-bacterial foaming hand soap

10.1 fl.oz

Made in China

Distributed by Jets, Sets & Elephants Beauty Corp.

For ShopKo Stores Operating Co., LLC

Green Bay, WI 54307, U.S.A

©2012 ShopKo Stores Operating Co., LLC

SATISFACTION GUARANTEED BY REFUND OR EXCHANGE

Bottle Label

PACKAGE/LABEL PRINCIPAL DISPLAY PANEL

bath·body·etc®

limited edition
autumn orange

anti-bacterial foaming hand soap

10.1 fl.oz

Made in China

Distributed by Jets, Sets & Elephants Beauty Corp.

For ShopKo Stores Operating Co., LLC

Green Bay, WI 54307, U.S.A

©2012 ShopKo Stores Operating Co., LLC

SATISFACTION GUARANTEED BY REFUND OR EXCHANGE

Bottle Label

PACKAGE/LABEL PRINCIPAL DISPLAY PANEL

bath·body·etc®

limited edition
enchanted woods

anti-bacterial foaming hand soap

10.1 fl.oz

Made in China

Distributed by Jets, Sets & Elephants Beauty Corp.

For ShopKo Stores Operating Co., LLC

Green Bay, WI 54307, U.S.A

©2012 ShopKo Stores Operating Co., LLC

SATISFACTION GUARANTEED BY REFUND OR EXCHANGE

Bottle Label